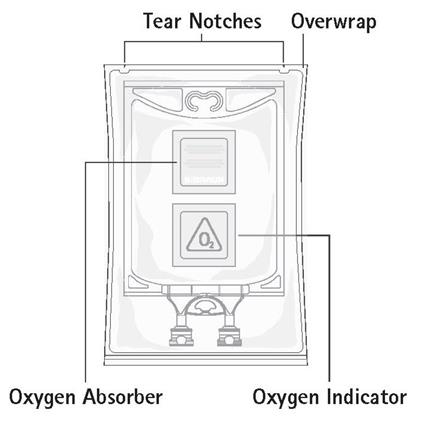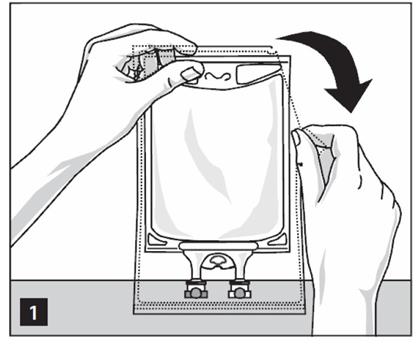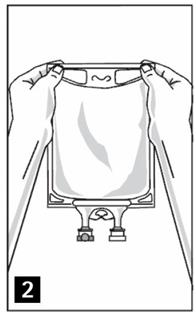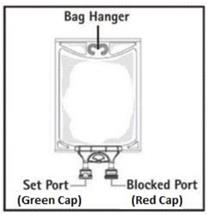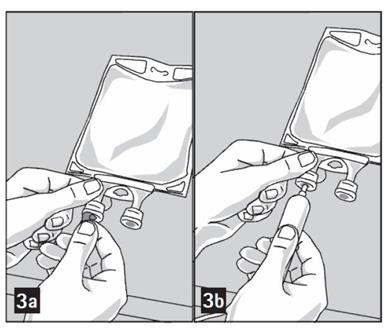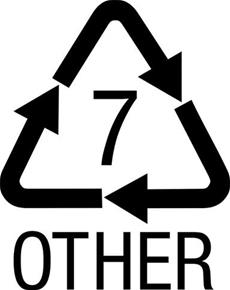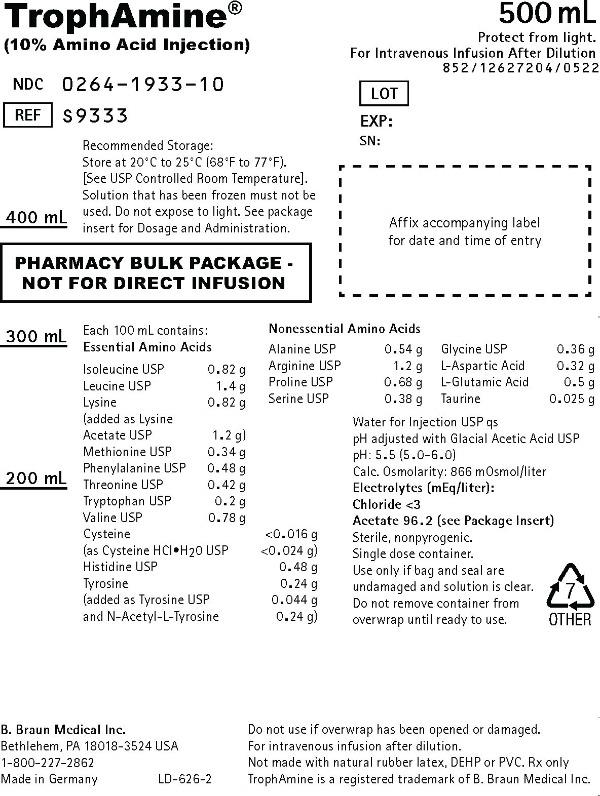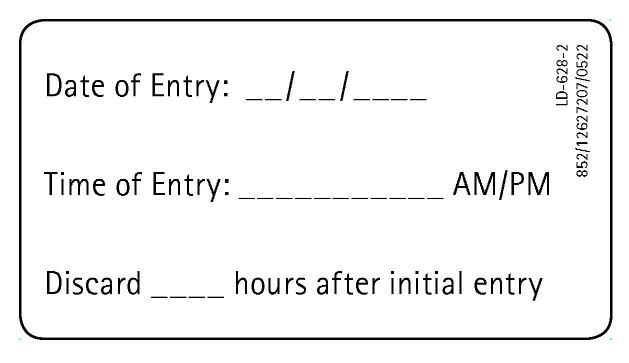 DRUG LABEL: TrophAmine
NDC: 0264-1933 | Form: SOLUTION
Manufacturer: B. Braun Medical Inc.
Category: prescription | Type: HUMAN PRESCRIPTION DRUG LABEL
Date: 20231127

ACTIVE INGREDIENTS: ISOLEUCINE 0.82 g/100 mL; LEUCINE 1.4 g/100 mL; LYSINE ACETATE 1.2 g/100 mL; METHIONINE 0.34 g/100 mL; PHENYLALANINE 0.48 g/100 mL; THREONINE 0.42 g/100 mL; TRYPTOPHAN 0.2 g/100 mL; VALINE 0.78 g/100 mL; CYSTEINE HYDROCHLORIDE 0.024 g/100 mL; HISTIDINE 0.48 g/100 mL; TYROSINE 0.044 g/100 mL; ACETYL L-TYROSINE 0.24 g/100 mL; ALANINE 0.54 g/100 mL; ARGININE 1.2 g/100 mL; PROLINE 0.68 g/100 mL; SERINE 0.38 g/100 mL; GLYCINE 0.36 g/100 mL; ASPARTIC ACID 0.32 g/100 mL; GLUTAMIC ACID 0.5 g/100 mL; TAURINE 0.025 g/100 mL
INACTIVE INGREDIENTS: WATER; ACETIC ACID

TrophAmine®
(Amino Acid Injection)

PHARMACY BULK PACKAGE –
NOT FOR DIRECT INFUSION

Protect from light.

DESCRIPTION

TrophAmine® (10% Amino Acid Injection) is a sterile, nonpyrogenic, hypertonic solution containing crystalline amino acids.

All amino acids designated USP are the “L”-isomer with the exception of Glycine USP, which does not have an isomer.

Each 100 mL contains:

Essential Amino Acids | 10%
Isoleucine USP | 0.82 g
Leucine USP | 1.4 g
Lysine | 0.82 g
(added as Lysine Acetate USP | 1.2 g)
Methionine USP | 0.34 g
Phenylalanine USP | 0.48 g
Threonine USP | 0.42 g
Tryptophan USP | 0.2 g
Valine USP | 0.78 g
Cysteine | <0.016 g
(as Cysteine HCl∙H2O USP | <0.024 g)
Histidine USP [Holt LE, Snyderman SE: The amino acid requirements of infants. JAMA 1961; 175(2):124–127.] | 0.48 g
Tyrosine | 0.24 g
(added as Tyrosine USP | 0.044 g
and N-Acetyl-L-Tyrosine | 0.24 g)
Nonessential Amino Acids
Alanine USP | 0.54 g
Arginine USP | 1.2 g
Proline USP | 0.68 g
Serine USP | 0.38 g
Glycine USP | 0.36 g
L-Aspartic Acid | 0.32 g
L-Glutamic Acid | 0.5 g
Taurine [Rigo J, Senterre J: Is taurine essential for the neonates? Biol Neonate 1977; 32:73–76.] [Gaull G, Sturman JA, Räihä NCR: Development of mammalian sulfur metabolism: Absence of cystothionase in human fetal tissues. Pediatr Res 1972; 6:538–547.] | 0.025 g
Water for Injection USP | qs
pH adjusted with Glacial Acetic Acid USP pH: 5.5 (5.0–6.0)
Calc. Osmolarity (mOsmol/liter) | 866
Total Amino Acids (grams/liter) | 100
Total Nitrogen (grams/liter) | 15.5
Protein Equivalent (grams/liter) | 97
Electrolytes (mEq/liter)
[Provided as acetic acid and lysine acetate.] Acetate (CH3COO^–) | 96.2
Chloride | <3

CLINICAL PHARMACOLOGY

TrophAmine® provides a mixture of essential and nonessential amino acids as well as taurine and a soluble form of tyrosine, N-Acetyl-L-Tyrosine (NAT). This amino acid composition has been specifically formulated to provide a well tolerated nitrogen source for nutritional support and therapy for infants and young pediatric patients. When administered in conjunction with cysteine hydrochloride, TrophAmine® results in the normalization of the plasma amino acid concentrations to a profile consistent with that of a breast-fed infant.

The rationale for TrophAmine® (Amino Acid Injection) is based on the observation of inadequate levels of essential amino acids in the plasma of infants receiving total parenteral nutrition (TPN) using conventional amino acid solutions. The TrophAmine® formula was developed through the application of specific pharmacokinetic multiple regression analysis relating amino acid intake to the resulting plasma amino acid concentrations.

Clinical studies in infants and young pediatric patients who required TPN therapy showed that infusion of TrophAmine® with a cysteine hydrochloride admixture resulted in a normalization of the plasma amino acid concentrations. In addition, weight gains, nitrogen balance, and serum protein concentrations were consistent with an improving nutritional status.

When infused with hypertonic dextrose as a calorie source, supplemented with cysteine hydrochloride, electrolytes, vitamins, and minerals, TrophAmine® provides total parenteral nutrition in infants and young pediatric patients, with the exception of essential fatty acids.

It is thought that the acetate from lysine acetate and acetic acid, under the conditions of parenteral nutrition, does not impact net acid-base balance when renal and respiratory functions are normal. Clinical evidence seems to support this thinking; however, confirmatory experimental evidence is not available.

The amount of chloride present in TrophAmine® is not of clinical significance.

The addition of cysteine hydrochloride will contribute to the chloride load.

The electrolyte content of any additives that are introduced should be carefully considered and included in total input computations.

INDICATIONS AND USAGE

TrophAmine® is indicated for the nutritional support of infants (including those of low birth weight) and young pediatric patients requiring TPN via either central or peripheral infusion routes. Parenteral nutrition with TrophAmine® is indicated to prevent nitrogen and weight loss or treat negative nitrogen balance in infants and young pediatric patients where (1) the alimentary tract, by the oral, gastrostomy, or jejunostomy route, cannot or should not be used, or adequate protein intake is not feasible by these routes; (2) gastrointestinal absorption of protein is impaired; or (3) protein requirements are substantially increased as with extensive burns. Dosage, route of administration, and concomitant infusion of non-protein calories are dependent on various factors, such as nutritional and metabolic status of the patient, anticipated duration of parenteral nutritional support, and vein tolerance. See WARNINGS, PRECAUTIONS, Pediatric Use, AND DOSAGE AND ADMINISTRATION.

Central Venous Nutrition

Central venous infusion should be considered when amino acid solutions are to be admixed with hypertonic dextrose to promote protein synthesis in hypercatabolic or severely depleted infants, or those requiring long-term parenteral nutrition.

Peripheral Parenteral Nutrition

For moderately catabolic or depleted patients in whom the central venous route is not indicated, diluted amino acid solutions mixed with 5-10% dextrose solutions may be infused by peripheral vein, supplemented, if desired, with fat emulsion. In pediatric patients, the final solution should not exceed twice normal serum osmolarity (718 mOsmol/L).

CONTRAINDICATIONS

TrophAmine® is contraindicated in patients with untreated anuria, hepatic coma, inborn errors of amino acid metabolism, including those involving branched chain amino acid metabolism such as maple syrup urine disease and isovaleric acidemia, or hypersensitivity to one or more amino acids present in the solution.

WARNINGS

Safe, effective use of parenteral nutrition requires a knowledge of nutrition as well as clinical expertise in recognition and treatment of the complications which can occur. Frequent clinical evaluation and laboratory determinations are necessary for proper monitoring of parenteral nutrition. Studies should include blood sugar, serum proteins, kidney and liver function tests, electrolytes, hemogram, carbon dioxide content, serum osmolalities, blood cultures, and blood ammonia levels.

WARNING: This product contains aluminum that may be toxic. Aluminum may reach toxic levels with prolonged parenteral administration if kidney function is impaired. Premature neonates are particularly at risk because their kidneys are immature, and they require large amounts of calcium and phosphate solutions, which contain aluminum.

Research indicates that patients with impaired kidney function, including premature neonates, who receive parenteral levels of aluminum at greater than 4 to 5 mcg/kg/day accumulate aluminum at levels associated with central nervous system and bone toxicity. Tissue loading may occur at even lower rates of administration.

Administration of amino acids in the presence of impaired renal function or gastrointestinal bleeding may augment an already elevated blood urea nitrogen. Patients with azotemia from any cause should not be infused with amino acids without regard to total nitrogen intake.

Administration of intravenous solutions can cause fluid and/or solute overload resulting in dilution of serum electrolyte concentrations, overhydration, congested states, or pulmonary edema. The risk of dilutional states is inversely proportional to the electrolyte concentrations of the solutions. The risk of solute overload causing congested states with peripheral and pulmonary edema is directly proportional to the electrolyte concentrations of the solutions.

Administration of amino acid solutions to a patient with hepatic insufficiency may result in plasma amino acid imbalances, hyperammonemia, prerenal azotemia, stupor and coma.

Hyperammonemia is of special significance in infants as its occurrence in the syndrome caused by genetic metabolic defects is sometimes associated, although not necessarily in a causal relationship, with mental retardation. This reaction appears to be dose related and is more likely to develop during prolonged therapy. It is essential that blood ammonia be measured frequently in infants. The mechanisms of this reaction are not clearly defined but may involve genetic defects and immature or subclinically impaired liver function.

Conservative doses of amino acids should be given, dictated by the nutritional status of the patient. Should symptoms of hyperammonemia develop, amino acid administration should be discontinued and the patient’s clinical status reevaluated.

PRECAUTIONS

General

Clinical evaluation and periodic laboratory determinations are necessary to monitor changes in fluid balance, electrolyte concentrations, and acid-base balance during prolonged parenteral therapy or whenever the condition of the patient warrants such evaluation. Significant deviations from normal concentrations may require the use of additional electrolyte supplements.

Strongly hypertonic nutrient solutions should be administered via an intravenous catheter placed in a central vein, preferably the superior vena cava.

Care should be taken to avoid circulatory overload, particularly in patients with cardiac insufficiency.

Special care must be taken when giving hypertonic dextrose to a diabetic or pre-diabetic patient. To prevent severe hyperglycemia in such patients, insulin may be required.

Administration of glucose at a rate exceeding the patient’s utilization rate may lead to hyperglycemia, coma, and death.

Administration of amino acids without carbohydrates may result in the accumulation of ketone bodies in the blood. Correction of this ketonemia may be achieved by the administration of carbohydrate.

Peripheral administration of TrophAmine® (Amino Acid Injection) requires appropriate dilution and provision of adequate calories. Care should be taken to assure proper placement of the needle within the lumen of the vein. The venipuncture site should be inspected frequently for signs of infiltration. If venous thrombosis or phlebitis occurs, discontinue infusions or change infusion site and initiate appropriate treatment. In pediatric patients, the final solution should not exceed twice normal serum osmolarity (718 mOsmol/L).

Extraordinary electrolyte losses such as may occur during protracted nasogastric suction, vomiting, diarrhea, or gastrointestinal fistula drainage may necessitate additional electrolyte supplementation.

Metabolic acidosis can be prevented or readily controlled by adding a portion of the cations in the electrolyte mixture as acetate salts and in the case of hyperchloremic acidosis, by keeping the total chloride content of the infusate to a minimum. TrophAmine® (Amino Acid Injection) contains less than 3 mEq chloride per liter.

TrophAmine® contains no added phosphorus. Patients, especially those with hypophosphatemia, may require the addition of phosphate. To prevent hypocalcemia, calcium supplementation should always accompany phosphate administration. To assure adequate intake, serum levels should be monitored frequently.

To minimize the risk of possible incompatibilities arising from mixing this solution with other additives that may be prescribed, the final infusate should be inspected for cloudiness or precipitation immediately after mixing, prior to administration, and periodically during administration.

Use only if solution is clear, the seal unbroken, and vacuum is present.

Drug product contains no more than 25 mcg/L of aluminum.

Laboratory Tests

Frequent clinical evaluation and laboratory determinations are necessary for proper monitoring during administration.

Laboratory tests should include measurement of blood sugar, electrolyte, and serum protein concentrations; kidney and liver function tests; and evaluation of acid-base balance and fluid balance. Other laboratory tests may be suggested by the patient’s condition.

Drug Interactions

Some additives may be incompatible. Consult with pharmacist. When introducing additives, use aseptic techniques. Mix thoroughly. Do not store.

Carcinogenesis, Mutagenesis, Impairment of Fertility

No in vitro or in vivo carcinogenesis, mutagenesis, or fertility studies have been conducted with TrophAmine®.

Pregnancy

Teratogenic Effects

Animal reproduction studies have not been conducted with TrophAmine® (Amino Acid Injection). It is also not known whether TrophAmine® can cause fetal harm when administered to a pregnant woman or can affect reproduction capacity. TrophAmine® should be given to a pregnant woman only if clearly needed.

Labor and Delivery

Information is unknown.

Nursing Mothers

It is not known whether this drug is excreted in human milk. Because many drugs are excreted in human milk, caution should be exercised with TrophAmine® if administered to a nursing woman.

Pediatric Use

As in all cases of fluid and electrolyte replacement and parenteral nutrition, careful monitoring and special caution is required in pediatric use, especially in pediatric patients with renal failure, acute sepsis, or low birth weight.

The total volume of nutritional fluid and the rate of administration in each patient will be based on individually calculated maintenance and/or replacement fluid requirements, and nutritional needs, and will vary with the child’s age, body weight and renal function.

In neonates and very small infants, particularly careful monitoring will be required to maintain fluid and electrolyte balance, including monitoring of blood glucose.

See INDICATIONS AND USAGE, WARNINGS, and DOSAGE AND ADMINISTRATION.

Geriatric Use

TrophAmine® has not been studied in geriatric patients. Elderly patients are known to be more prone to fluid overload and electrolyte imbalance than younger patients. This may be related to impairment of renal function which is more frequent in an elderly population. As a result the need for careful monitoring of fluid and electrolyte therapy is greater in the elderly.

All patients, including the elderly, require an individual dose of all parenteral nutrition products to be determined by the physician on an individual case-by-case basis, which will be based on body weight, clinical condition and the results of laboratory monitoring tests. There is no specific geriatric dose.

See WARNINGS.

Special Precautions for Central Venous Nutrition

Administration by central venous catheter should be used only by those familiar with this technique and its complications.

Central venous nutrition may be associated with complications which can be prevented or minimized by careful attention to all aspects of the procedure, including solution preparation, administration, and patient monitoring. It is essential that a carefully prepared protocol, based on current medical practices, be followed, preferably by an experienced team.

Although a detailed discussion of the complications is beyond the scope of this insert, the following summary lists those based on current literature:

Technical. The placement of a central venous catheter should be regarded as a surgical procedure. One should be fully acquainted with various techniques of catheter insertion as well as recognition and treatment of complications. For details of techniques and placement sites, consult the medical literature. X-ray is the best means of verifying catheter placement. Complications known to occur from the placement of central venous catheters are pneumothorax, hemothorax, hydrothorax, artery puncture and transection, injury to the brachial plexus, malposition of the catheter, formation of arteriovenous fistula, phlebitis, thrombosis, and air and catheter embolus.

Septic. The constant risk of sepsis is present during central venous nutrition. Since contaminated solutions and infusion catheters are potential sources of infection, it is imperative that the preparation of parenteral nutrition solutions and the placement and care of catheters be accomplished under controlled aseptic conditions.

Solutions should ideally be prepared in the hospital pharmacy in a laminar flow hood. The key factor in their preparation is careful aseptic technique to avoid inadvertent touch contamination during mixing of solutions and subsequent admixtures.

Parenteral nutrition solutions should be used promptly after mixing. Any storage should be under refrigeration for as brief a time as possible. Administration time for a TPN solution should not exceed 24 hours.

Consult the medical literature for a discussion of the management of sepsis during central venous nutrition. In brief, typical management includes replacing the solution being administered with a fresh container and set, and the remaining contents are cultured for bacterial or fungal contamination. If sepsis persists and another source of infection is not identified, the catheter is removed, the proximal tip cultured, and a new catheter reinserted when the fever has subsided. Non-specific, prophylactic antibiotic treatment is not recommended. Clinical experience indicates that the catheter is likely to be the prime source of infection as opposed to aseptically prepared and properly stored solutions.

Metabolic. The following metabolic complications have been reported: metabolic acidosis, hypophosphatemia, alkalosis, hyperglycemia and glycosuria, osmotic diuresis and dehydration, rebound hypoglycemia, elevated liver enzymes, hypo- and hypervitaminosis, electrolyte imbalances, and hyperammonemia in pediatric patients. Frequent clinical evaluation and laboratory determinations are necessary, especially during the first few days of venous nutrition, to prevent or minimize these complications.

ADVERSE REACTIONS

See “WARNINGS” and “Special Precautions for Central Venous Nutrition.”

Reactions reported in clinical studies as a result of infusion of the parenteral fluid were water weight gain, edema, increase in BUN, and mild acidosis.

Reactions which may occur because of the solution or the technique of administration include febrile response, infection at the site of injection, venous thrombosis or phlebitis extending from the site of injection, extravasation and hypervolemia.

Local reaction at the infusion site, consisting of a warm sensation, erythema, phlebitis and thrombosis, have been reported with peripheral amino acid infusions, especially if other substances are also administered through the same site.

If electrolyte supplementation is required during peripheral infusion, it is recommended that additives be administered throughout the day in order to avoid possible venous irritation. Irritating additive medications may require injection at another site and should not be added directly to the amino acid infusate.

Symptoms may result from an excess or deficit of one or more of the ions present in the solution; therefore, frequent monitoring of electrolyte levels is essential.

Phosphorus deficiency may lead to impaired tissue oxygenation and acute hemolytic anemia. Relative to calcium, excessive phosphorus intake can precipitate hypocalcemia with cramps, tetany and muscular hyperexcitability.

If an adverse reaction does occur, discontinue the infusion, evaluate the patient, institute appropriate therapeutic countermeasures and save the remainder of the fluid for examination if deemed necessary.

OVERDOSAGE

In the event of a fluid or solute overload during parenteral therapy, reevaluate the patient’s condition, and institute appropriate corrective treatment.

DOSAGE AND ADMINISTRATION

The objective of nutritional management of infants and young pediatric patients is the provision of sufficient amino acid and caloric support for protein synthesis and growth.

The total daily dose of TrophAmine® (Amino Acid Injection) depends on daily protein requirements and on the patient’s metabolic and clinical response. The determination of nitrogen balance and accurate daily body weights, corrected for fluid balance, are probably the best means of assessing individual protein requirements. Dosage should also be guided by the patient’s fluid intake limits and glucose and nitrogen tolerances, as well as by metabolic and clinical response.

Recommendations for allowances of protein in infant nutrition have ranged from 2 to 4 grams of protein per kilogram of body weight per day (2 to 4 g/kg/day). [Suskind RM: Textbook of Pediatric Nutrition, Raven Press, New York, 1981.] The recommended dosage of TrophAmine® is 2 to 2.5 grams of amino acids per kilogram of body weight per day (2 to 2.5 g/kg/day) for infants up to 10 kilograms. For infants and young pediatric patients larger than 10 kilograms, the total dosage of amino acids should include the 20 to 25 grams/day for the first 10 kg of body weight plus 1 to 1.25 g/day for each kg of body weight over 10 kilograms.

Typically, TrophAmine® is admixed with 50% or 70% Dextrose Injection USP supplemented with electrolytes and vitamins and administered over a period of time not to exceed 24 hours.

Total daily fluid intake should be appropriate for the patient’s age and size. A fluid dose of 125 mL per kilogram body weight per day is appropriate for most infants on TPN. Although nitrogen requirements may be higher in severely hypercatabolic or depleted patients, provision of additional nitrogen may not be possible due to fluid intake limits, nitrogen, or glucose intolerance.

Cysteine is considered to be an essential amino acid in infants and young pediatric patients. An admixture of cysteine hydrochloride to the TPN solution is therefore recommended. Based on clinical studies, the recommended dosage is 1 mmole of L-cysteine hydrochloride monohydrate per kilogram of body weight per day.

In many patients, provision of adequate calories in the form of hypertonic dextrose may require the administration of exogenous insulin to prevent hyperglycemia and glycosuria. To prevent rebound hypoglycemia, a solution containing 5% dextrose should be administered when hypertonic dextrose solutions are abruptly discontinued.

Fat emulsion coadministration should be considered when prolonged (more than 5 days) parenteral nutrition is required in order to prevent essential fatty acid deficiency (E.F.A.D.). Serum lipids should be monitored for evidence of E.F.A.D. in patients maintained on fat free TPN.

The provision of sufficient intracellular electrolytes, principally potassium, magnesium, and phosphate, is required for optimum utilization of amino acids. In addition, sufficient quantities of the major extracellular electrolytes sodium, calcium, and chloride, must be given. In patients with hyperchloremic or other metabolic acidoses, sodium and potassium may be added as the acetate salts to provide bicarbonate precursor. The electrolyte content of TrophAmine® must be considered when calculating daily electrolyte intake. Serum electrolytes, including magnesium and phosphorus, should be monitored frequently.

Appropriate vitamins, minerals and trace elements should also be provided.

Central Venous Nutrition. Hypertonic mixtures of amino acids and dextrose may be safely administered by continuous infusion through a central venous catheter with the tip located in the superior vena cava. Initial infusion rates should be slow, and gradually increased to the recommended 60-125 mL per kilogram body weight per day. If administration rate should fall behind schedule, no attempt to “catch up” to planned intake should be made. In addition to meeting protein needs, the rate of administration, particularly during the first few days of therapy, is governed by the patient’s glucose tolerance. Daily intake of amino acids and dextrose should be increased gradually to the maximum required dose as indicated by frequent determinations of glucose levels in blood and urine.

Use of an infusion pump is advisable to maintain a steady infusion rate during central venous infusion.

Peripheral Parenteral Nutrition. For patients in whom the central venous route is not indicated and who can consume adequate calories enterally, TrophAmine® (Amino Acid Injection) may be administered by peripheral vein with or without parenteral carbohydrate calories. Such infusates can be prepared by dilution with B. Braun’s Sterile Water for Injection or 5%-10% Dextrose Injection to prepare isotonic or slightly hypertonic solutions for peripheral infusion. It is essential that peripheral infusion be accompanied by adequate caloric intake. In pediatric patients, the final solution should not exceed twice normal serum osmolarity (718 mOsmol/L).

Parenteral drug products should be inspected visually for particulate matter and discoloration prior to administration, whenever solution and container permit.

TrophAmine® may be admixed with solutions which contain phosphate or which have been supplemented with phosphate. The presence of calcium and magnesium ions in an additive solution should be considered when phosphate is also present, in order to avoid precipitation.

Care must be taken to avoid incompatible admixtures. Consult with pharmacist.

HOW SUPPLIED

TrophAmine® pharmacy bulk package is supplied sterile and nonpyrogenic in 500 mL flexible plastic bags, packaged 12 per case.

NDC | REF | Size
0264-1933-10 | S9333 | 500 mL

Not made with natural rubber latex, DEHP or PVC.

Storage

Store in the closed corrugated case; do not expose TrophAmine® and/or TrophAmine®-containing admixed parenteral nutrition (PN) solution to light. Do not remove container from overwrap until ready to use. Do not use if overwrap has been opened or damaged. Exposure of pharmaceutical products to heat should be minimized. Avoid excessive heat. It is recommended that the product be stored at 20°C to 25°C (68°F to 77°F); excursions permitted between 15°C to 30°C (59°F to 86°F). [See USP Controlled Room Temperature]. Solution that has been frozen must not be used.

Rx only

TrophAmine is a registered trademark of B. Braun Medical Inc.

Preparation Instructions for TrophAmine®

Caution: TrophAmine® Pharmacy Bulk Package is intended for intravenous infusion after further dilution only.

Do not expose TrophAmine® and/or TrophAmine®-containing admixed parenteral nutrition (PN) solution to light.

The pharmacy bulk package is for use in a Pharmacy Admixture Service only. Use of this product is restricted to a suitable work area, such as a laminar flow hood (or an equivalent clean air compounding area).

Designed for use with an unvented sterile dispensing set.

Step 1: Inspect Pharmacy Bulk Package overwrap and primary bag and do not use if damaged. Inspect oxygen indicator and do not use if oxygen indicator is pink or dark pink. Use only if container and seals are intact.

Step 2: To open, tear overwrap starting from the tear notches (Figure 1). Remove TrophAmine® Pharmacy Bulk Package bag from overwrap and discard oxygen indicator, oxygen absorber and overwrap.

Step 3: Inspect TrophAmine® Pharmacy Bulk Package bag visually (Figure 2). Parenteral drug products should be inspected visually for particulate matter and discoloration prior to administration, whenever solution and container permit. Inspect TrophAmine® for cloudiness, haze or particulate matter in good lighting. Discard the bag if any particulates or discoloration are observed.

Step 4: Remove aluminum foil of set port at the bottom of the Pharmacy Bulk Package bag (Figure 3a) and attach an unvented sterile dispensing set (Figure 3b).

The set port may be penetrated only one time, utilizing a suitable sterile dispensing set which allows measured dispensing of the contents.

The withdrawal of container contents should be accomplished without delay using aseptic technique. Discard container no later than 4 hours after initial closure puncture.

Use of a syringe with needle is not recommended. Multiple entries increase the potential of the microbial and particulate contamination.

B. Braun Medical Inc.
Bethlehem, PA 18018-3524 USA
1-800-227-2862
Made in Germany

Revised: June 2022

LD-625-2

PRINCIPAL DISPLAY PANEL - 500 mL Container Label

TrophAmine®
(10% Amino Acid Injection)

NDC 0264-1933-10

REF S9333

500 mL

Protect from light.

For Intravenous Infusion After Dilution

852/12627204/0522

LOT
EXP:
SN:

Recommended Storage: Store at 20°C to 25°C (68°F to 77°F). [See USP Controlled Room Temperature]. Solution that has been frozen must not be used. Do not expose to light. See package insert for Dosage and Administration.

PHARMACY BULK PACKAGE -
NOT FOR DIRECT INFUSION

Each 100 mL contains:

Essential Amino Acids
Isoleucine USP | 0.82 g
Leucine USP | 1.4 g
Lysine | 0.82 g
(added as Lysine Acetate USP | 1.2 g)
Methionine USP | 0.34 g
Phenylalanine USP | 0.48 g
Threonine USP | 0.42 g
Tryptophan USP | 0.2 g
Valine USP | 0.78 g
Cysteine | <0.016 g
(as Cysteine HCI•H20 USP | <0.024 g)
Histidine USP | 0.48 g
Tyrosine | 0.24 g
(added as Tyrosine USP | 0.044 g
and N-Acetyl-L-Tyrosine | 0.24 g)

Affix accompanying label for date and time of entry

Nonessential Amino Acids
Alanine USP | 0.54 g
Arginine USP | 1.2 g
Proline USP | 0.68 g
Serine USP | 0.38 g
Glycine USP | 0.36 g
L-Aspartic Acid | 0.32 g
L-Glutamic Acid | 0.5 g
Taurine | 0.025 g

Water for Injection USP qs
pH adjusted with Glacial Acetic Acid USP
pH: 5.5 (5.0-6.0)
Calc. Osmolarity: 866 mOsmol/liter

Electrolytes (mEq/liter):
Chloride <3
Acetate 96.2 (see Package Insert)

Sterile, nonpyrogenic.
Single dose container.
Use only if bag and seal are undamaged and solution is clear.
Do not remove container from overwrap until ready to use.

Do not use if overwrap has been opened or damaged.
For intravenous infusion after dilution.
Not made with natural rubber latex, DEHP or PVC.
Rx only
TrophAmine is a registered trademark of B. Braun Medical Inc.

B. Braun Medical Inc.
Bethlehem, PA 18018-3524 USA
1-800-227-2862
Made in Germany

LD-626-2

PRINCIPAL DISPLAY PANEL - Accompanying 500 mL Bag Label

Date of Entry:___/____/_____

Time of Entry:____________________AM/PM

Discard______hours after initial entry

LD-628-2

852/12627207/0522